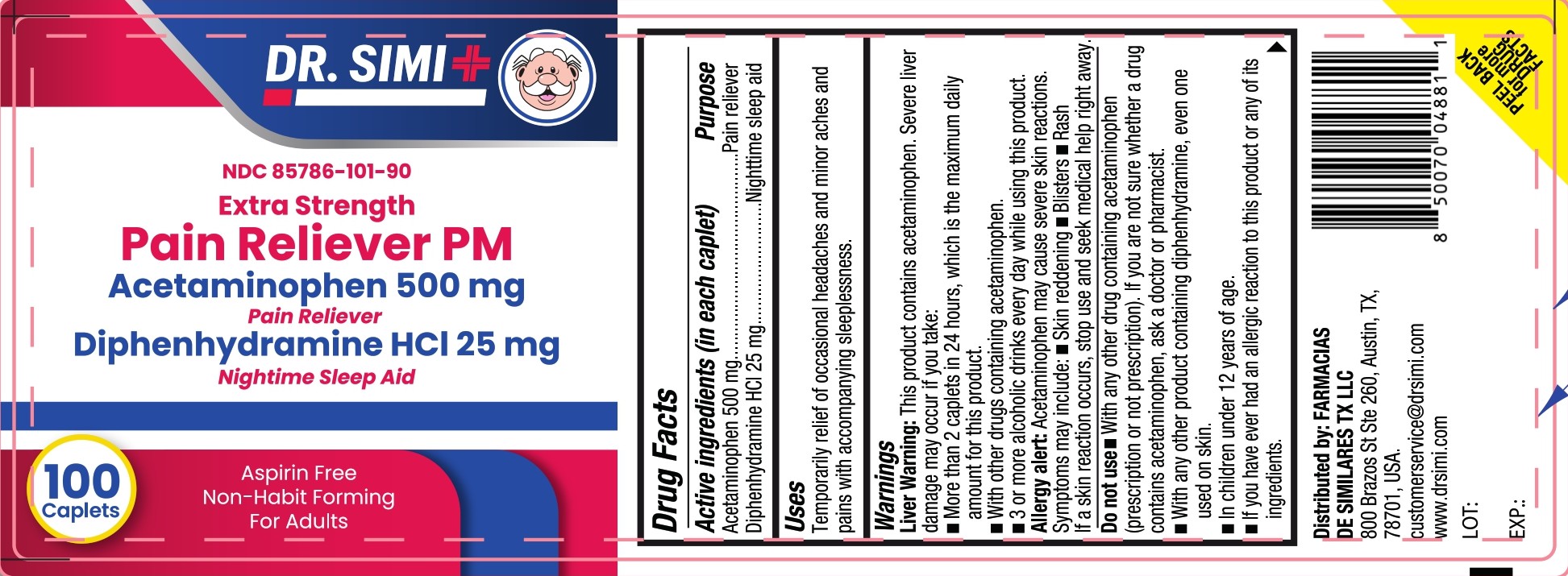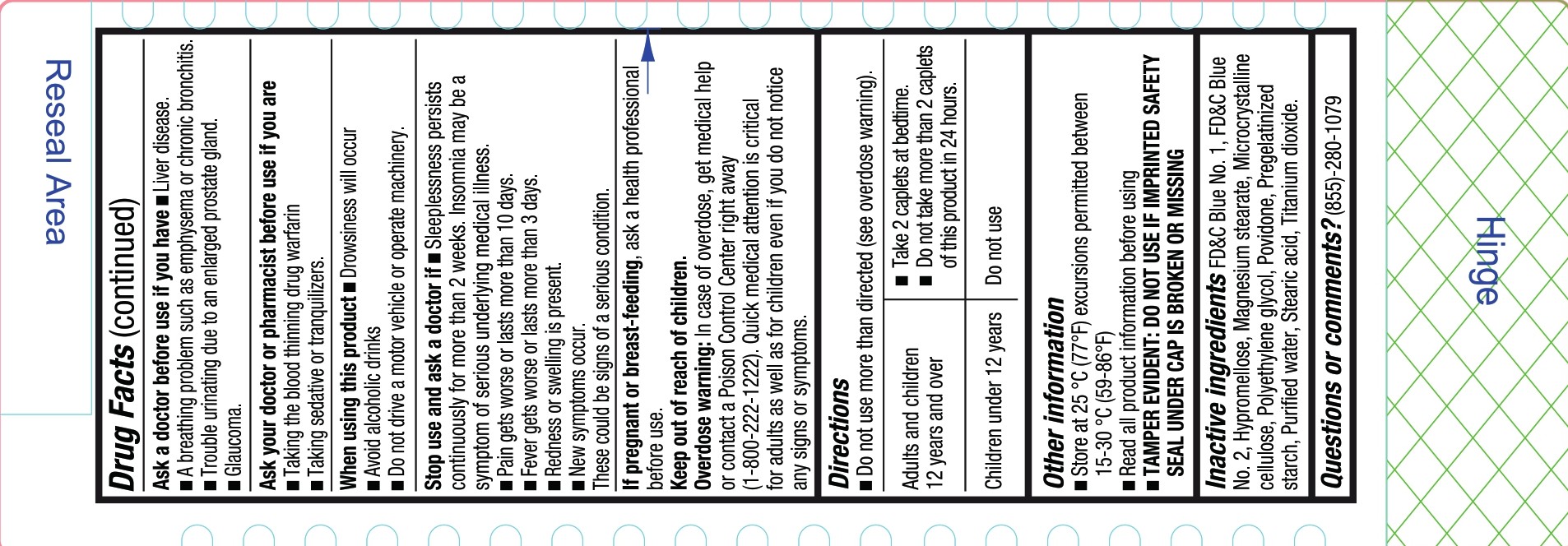 DRUG LABEL: Dr Simi Pain Reliever PM
NDC: 85786-101 | Form: TABLET, COATED
Manufacturer: Farmacias De Similares TX LLC
Category: otc | Type: HUMAN OTC DRUG LABEL
Date: 20250811

ACTIVE INGREDIENTS: ACETAMINOPHEN 500 mg/1 1; DIPHENHYDRAMINE HYDROCHLORIDE 25 mg/1 1
INACTIVE INGREDIENTS: FD&C BLUE NO. 1; STARCH, CORN; WATER; FD&C BLUE NO. 2; STEARIC ACID; HYPROMELLOSE, UNSPECIFIED; MICROCRYSTALLINE CELLULOSE; POLYETHYLENE GLYCOL, UNSPECIFIED; MAGNESIUM STEARATE; POVIDONE K30; TITANIUM DIOXIDE

Extra Strength Pain Reliever PM

Drug Facts

Active ingredients (in each caplet)

- Acetaminophen 500 mg
- Diphenhydramine HCl 25 mg

Pupose

- Pain reliever
- Nighttime sleep aid

Uses

Temporarily relief of occasional headaches and minor aches and pains with accompanying sleeplessness.

Warnings

WARNINGS

Liver warning: This product contains acetaminophen. Severe liver damage may occur if you take.

- More than 2 caplets in 24 hours, which is the maximum daily amount for this product.
- With other drugs containing acetaminophen.
- 3 or more alcoholicdrinks everyday while using this product.

Allergy alert: Acetaminophen may cause severe skin reactions. Symptoms may include:

- Skin reddening
- Blisters
- Rash

If a skin reaction occurs, stop use and seek medical help right away.

Do not use

- With any other drug containing acetaminophen (prescription or not prescription). If you are not sure whether a drug contains acetaminophen, ask a doctor or pharmacist.
- With any other product containing diphenhydramine, even one used on skin.
- In children under 12 years of age.
- If you have ever had an allergic reaction to this product or any of its ingredients.

Ask a doctor before use if you have

- Liver disease.
- A breathing problem such as emphysema or chronic bronchitis.
- Trouble urinating due to an enlarged prostate gland.
- Glaucoma.

Ask your doctor or pharmacist before use if you are

- Taking the blood thinning drug warfarin
- Taking sedative or tranquilizers.

When using this product

- Drowsiness will occur
- Avoid alcoholic drinks
- Do not drive a motor vehicle or operate machinery.

Stop use and ask a doctor if

- Sleeplessness persists continuously for more than 2 weeks. Insomnia may be a symptom of serious underlying medical illness.
- Pain gets worse or lasts more than 10 days.
- Fever gets worse or lasts more than 3 days.
- Redness or swelling is present.
- New symptoms occur.

These could be signs of a serious condition.

If pregnant or breast-feeding,

ask a health professional before use.

Keep out of reach of children.

Overdose warning:

In case of overdose, get medical help or contact a Poison Control Center right away. (1-800-222-1222) Quick medical attention is critical for adults as well as for children even if you do not notice any signs or symptoms.

Directions

- Do not use more than directed (see overdose warning).

Directions

Adults and children 12 years and over | - Take 2 caplets at bedtime. - Do not take more than 2 caplets of this product in 24 hours.
Children under 12 years | Do not use

Other information

- Store at 25 °C (77°F) excursions permitted between 15-30°C (59-86°F)
- Read all product information before using.
- TAMPER EVIDENT: DO NOT USE IF IMPRINTED SAFETY SEAL UNDER CAP IS BROKEN OR MISSING

Inactive ingredients

FD&C Blue No. 1, FD&C Blue No. 2, Hypromellose, Magnesium stearate, Microcrystalline cellulose, Polyethylene glycol, Povidone, Pregelatinized starch, Purified water, Stearic Acid, Titanium dioxide.

Questions or comments?

(855)-280-1079

Distributed by: FARMACIAS DE SIMILARES TX, LLC

800 Brazos St Ste 260, Austin, TX,

78701, USA.

customerservice@drsimi.com

www.drsimi.com

LOT:

EXP:

PEEL BACK for more DRUG FACTS

PACKAGE LABEL

DR SIMI

NDC 85786-101-90

Extra Strength

Pain Reliver PM

Acetaminophen 500 mg

Pain Reliever

Diphenhydramine HCl 25 mg

Nightime Sleep Aid

100 Caplets

Aspirin Free

Non-Habit Forming

For Adults